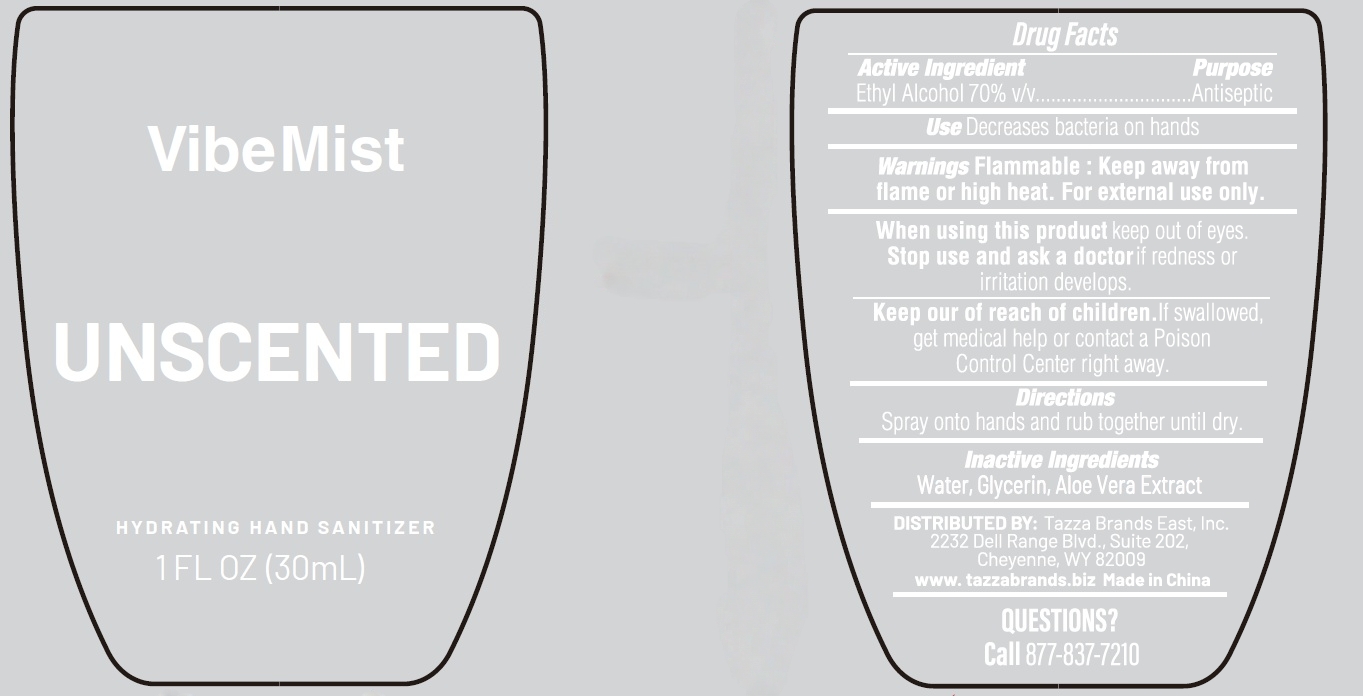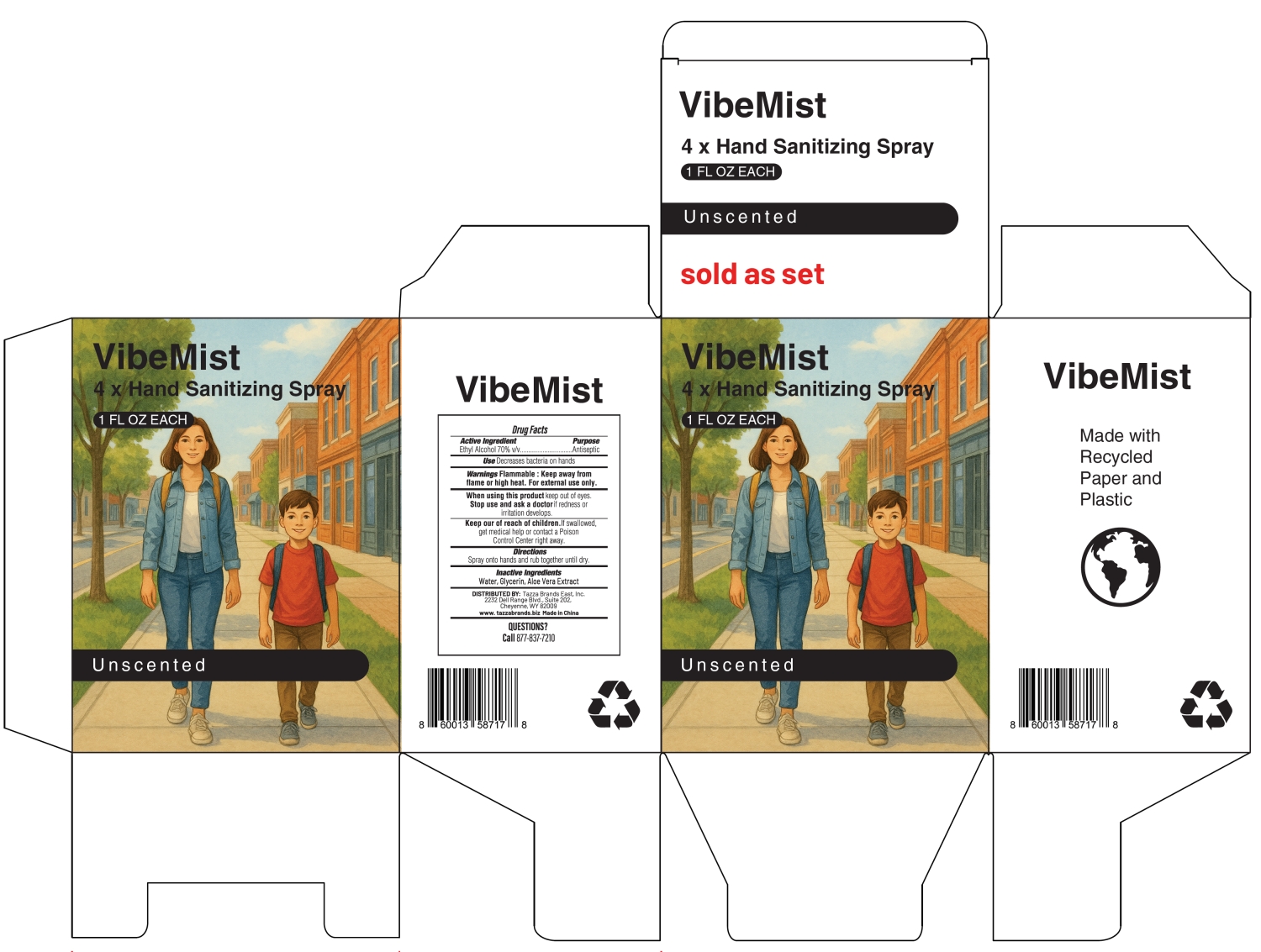 DRUG LABEL: VibeMist HYDRATING HAND SANITIZER UNSCENTED
NDC: 76370-0038 | Form: LIQUID
Manufacturer: Tazza Brands East Inc.
Category: otc | Type: HUMAN OTC DRUG LABEL
Date: 20251225

ACTIVE INGREDIENTS: ALCOHOL 70 mL/100 mL
INACTIVE INGREDIENTS: WATER; GLYCERIN; ALOE VERA LEAF

76370-0038 VibeMist HYDRATING HAND SANITIZER UNSCENTED

Active Ingredient

Ethyl Alcohol 70% v/v

Purpose

Antiseptic

INDICATIONS AND USAGE

Uses Decreases bacteria on hands

WARNINGS

Warnings Flammable: Keep away from flame or high heat. For external use only.

When using this product keep out of eyes.

Stop use and ask a doctor if redness or irritation develops.

Keep out of reach of children. If swallowed, get medical help or contact a Poison Control Center right away.

Directions

Spray onto hand and rub together until dry.

Inactive Ingredients

Water, Glycerin, Aloe Vera Extract, Fragrance

PACKAGE LABEL

VibeMist

UNSCENTED

HYDRATING HAND SANITIZER

1 FL OZ (30mL)

NDC: 76370-0038-0

VibeMist

4 × Hand Sanitizing Spray

1 FL OZ EACH

Unscented

sold as set

NDC: 76370-0038-1